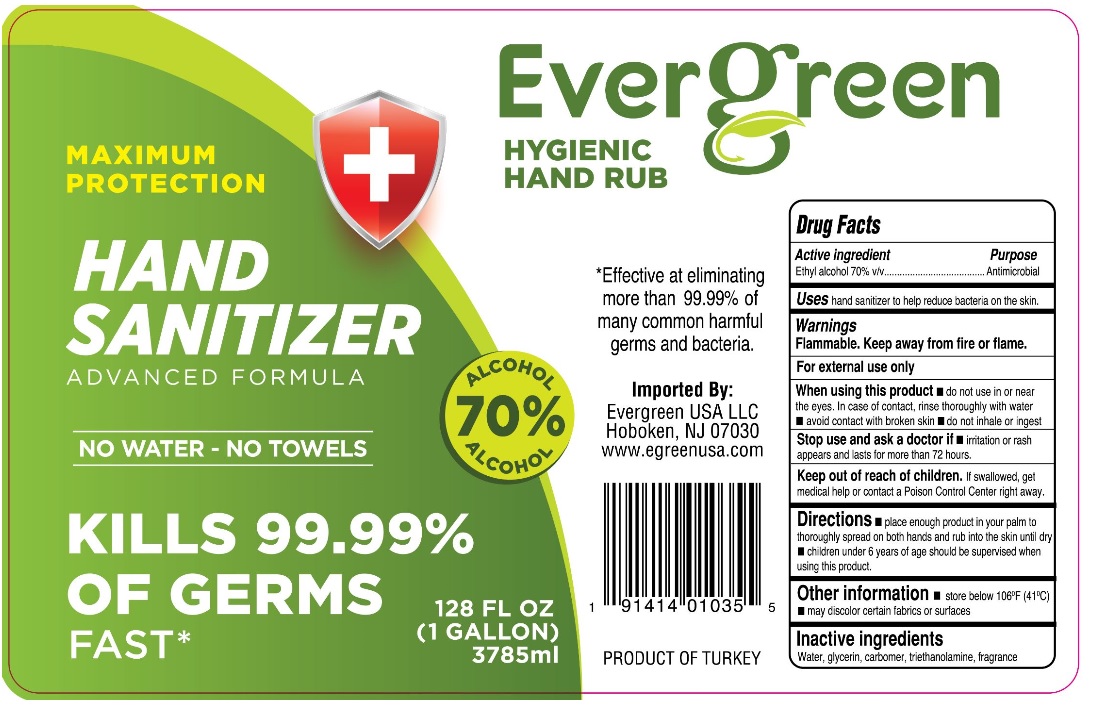 DRUG LABEL: Evergreen
NDC: 74600-004 | Form: LIQUID
Manufacturer: GENC GIDA KOZMETIK VE KIMYASAL URUNLER SANAYI VE TICARET LIMITED SIRKETI
Category: otc | Type: HUMAN OTC DRUG LABEL
Date: 20200529

ACTIVE INGREDIENTS: ALCOHOL 70 mL/100 mL
INACTIVE INGREDIENTS: WATER; GLYCERIN; CARBOMER HOMOPOLYMER, UNSPECIFIED TYPE; TROLAMINE

Evergreen HAND SANTIZER ADVANCED FORMULA

Active ingredient

Ethyl alcohol 70% v/v

Purpose

Antimicrobial

INDICATIONS AND USAGE

Uses hand sanitizer to help reduce bacteria on the skin.

Warnings

Flammable. Keep away from fire or flame.

For external use only

When using this product ■ do not use in or near the eyes. In case of contact, rinse thoroughly with water ■ avoid contact with broken skin ■ do not inhale or ingest
Stop use and ask a doctor if ■ irritation or rash appears and lasts for more than 72 hours.

Keep out of reach of children. If swallowed, get medical help or contact a Poison Control Center right away.

DOSAGE AND ADMINISTRATION

Directions ■ place enough product in your palm to thoroughly spread on both hands and rub into the skin until dry ■ children under 6 years of age should be supervised when using this product.

Other information ■ store below 106°F (41°C) ■ may discolor certain fabrics or surfaces

Inactive ingredients

Water, glycerin, carbomer, triethanolamine, fragrance

HYGIENIC HAND RUB

MAXIMUM PROTECTION

NO WATER - NO TOWELS

KILLS 99.99% OF GERMS

FAST*

*Effective at eliminating more than 99.99% of many common harmful germs and bacteria.

Imported by:

Evergreen USA LLC Hoboken, NJ 07030

www.egreenusa.com

PRODUCT OF TURKEY